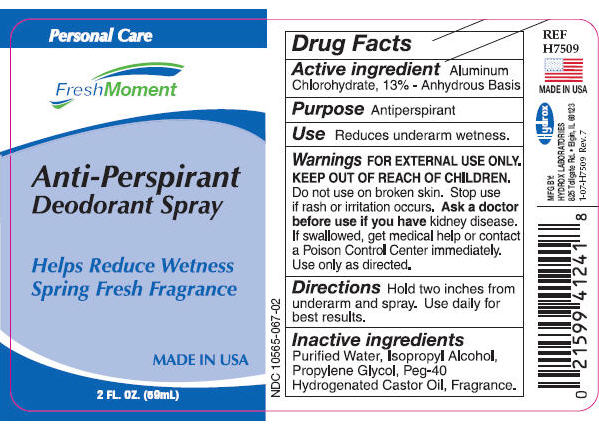 DRUG LABEL: Anti-Perspirant Deodorant
NDC: 10565-067 | Form: SPRAY
Manufacturer: Hydrox Laboratories
Category: otc | Type: HUMAN OTC DRUG LABEL
Date: 20260112

ACTIVE INGREDIENTS: ALUMINUM CHLOROHYDRATE 13 g/100 mL
INACTIVE INGREDIENTS: WATER; ISOPROPYL ALCOHOL; PROPYLENE GLYCOL; POLYOXYL 40 HYDROGENATED CASTOR OIL

Anti-Perspirant
Deodorant Spray

Drug Facts

Active ingredient

Aluminum Chlorohydrate, 13% - Anhydrous Basis

Purpose

Antiperspirant

Use

Reduces underarm wetness.

Warnings

FOR EXTERNAL USE ONLY.

KEEP OUT OF REACH OF CHILDREN.

Do not use on broken skin.

Stop use if rash or irritation occurs.

Ask a doctor before use if you havekidney disease.

WHEN USING

If swallowed, get medical help or contact a Poison Control Center immediately. Use only as directed.

Directions

Hold two inches from underarm and spray. Use daily for best results.

Inactive ingredients

Purified Water, Isopropyl Alcohol, Propylene Glycol, Peg-40 Hydrogenated Castor Oil, Fragrance.

MFG BY:
HYDROX LABORATORIES
825 Tollgate Rd. • Elgin, IL 60123

PRINCIPAL DISPLAY PANEL

Personal Care

FreshMoment

Anti-Perspirant
Deodorant Spray

Helps Reduce Wetness
Spring Fresh Fragrance

MADE IN USA

2 FL. OZ. (59mL)